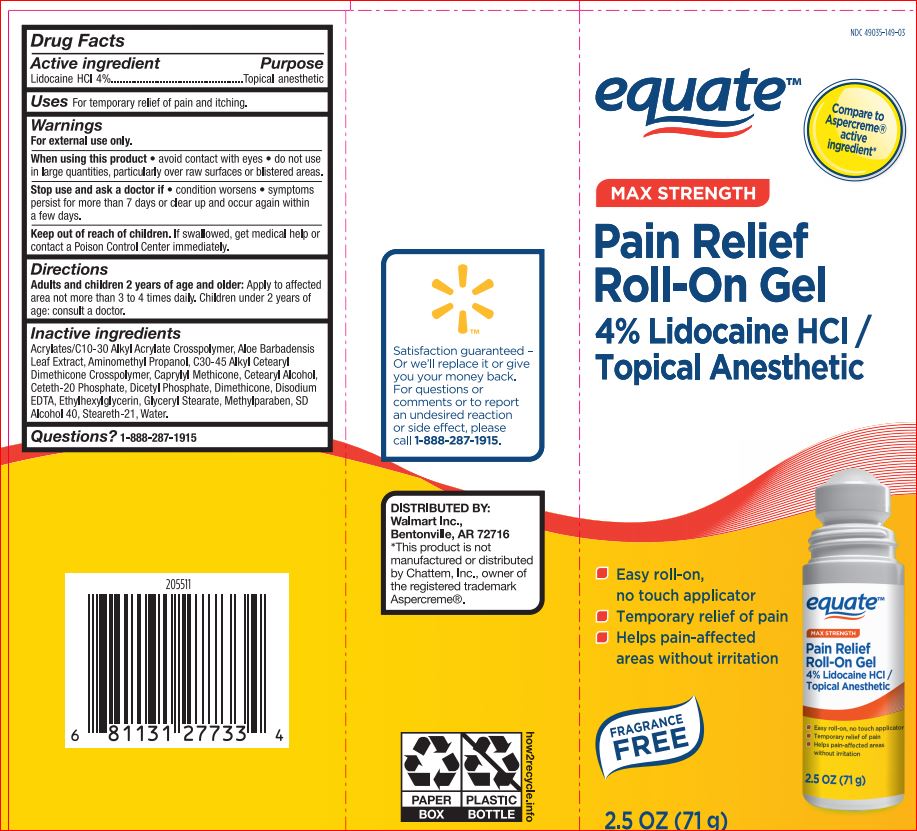 DRUG LABEL: Pain Relief
NDC: 49035-149 | Form: GEL
Manufacturer: Walmart
Category: otc | Type: HUMAN OTC DRUG LABEL
Date: 20180711

ACTIVE INGREDIENTS: LIDOCAINE HYDROCHLORIDE 4 g/100 mL
INACTIVE INGREDIENTS: ALOE VERA LEAF; AMINOMETHYLPROPANOL; CAPRYLYL TRISILOXANE; CETOSTEARYL ALCOHOL; Ceteth-20 Phosphate; DIHEXADECYL PHOSPHATE; Dimethicone; EDETATE DISODIUM; Ethylhexylglycerin; GLYCERYL MONOSTEARATE; Methylparaben; ALCOHOL; Steareth-21; WATER

EQT - Drug Facts

Active ingredient Purpose
Lidocaine HCl 4%..............................................Topical analgesic

INDICATIONS AND USAGE

Uses For temporary relief of pain and itching

Warnings
For external use only.
When using this product • use only as directed • do not bandage tightly • avoid contact with eyes • do not apply to wounds or damaged skin • do not use in large quantities, particularly over raw surfaces or blistered areas.
Stop use and ask a doctor if • condition worsens • symptoms persist for more than 7 days or clear up and occur again within a few days

Keep out of reach of children. If swallowed, get medical help or contact a Poison Control Center immediately

Directions
Adults and children 2 years of age and older: Apply to affected area not more than 3 to 4 times daily. Children under 2 years of age: consult a doctor.

Inactive ingredients
Acrylates/C10-30 Alkyl Acrylate Crosspolymer, Aloe Barbadensis
Leaf Juice, Aminomethyl Propanol, C30-45 Alkyl Cetearyl
Dimethicone Crosspolymer, Caprylyl Methicone, Cetearyl Alcohol,
Ceteth-20 Phosphate, Dicetyl Phosphate, Dimethicone, Disodium
EDTA, Ethylhexylglycerin, Glyceryl Stearate, Methylparaben, SD
Alcohol 40, Steareth-21, Water.